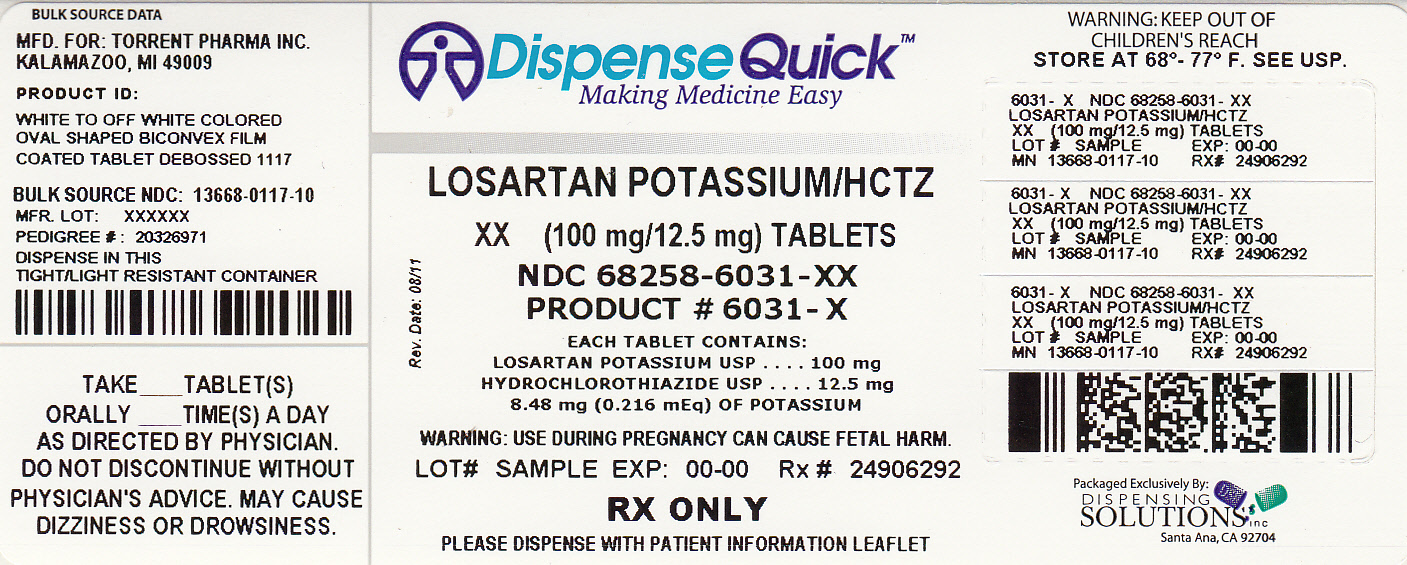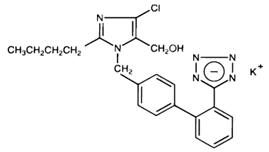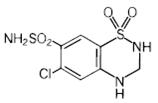 DRUG LABEL: Losartan Potassium and Hydrochlorothiazide
NDC: 68258-6031 | Form: TABLET
Manufacturer: Dispensing Solutions, Inc.
Category: prescription | Type: HUMAN PRESCRIPTION DRUG LABEL
Date: 20120217

ACTIVE INGREDIENTS: LOSARTAN POTASSIUM 100 mg/1 1; HYDROCHLOROTHIAZIDE 12.5 mg/1 1

BOXED WARNING

USE IN PREGNANCY

When used in pregnancy during the second and third trimesters, drugs that act directly on the renin-angiotensin system can cause injury and even death to the developing fetus. When pregnancy is detected, Losartan Potassium and Hydrochlorothiazide Tablets should be discontinued as soon as possible. See WARNINGS, Fetal/Neonatal Morbidity and Mortality.

DESCRIPTION

Losartan Potassium and Hydrochlorothiazide 50 mg/12.5 mg, Losartan Potassium and Hydrochlorothiazide 100 mg/12.5 mg and Losartan Potassium and Hydrochlorothiazide 100 mg/25 mg combine an angiotensin II receptor (type AT1) antagonist and a diuretic, hydrochlorothiazide.
Losartan potassium, a non-peptide molecule, is chemically described as 2-butyl-4-chloro-1-[p-(o-1H-tetrazol-5-ylphenyl)benzyl]imidazole-5-methanol monopotassium salt. Its empirical formula is C22H22ClKN6O, and its structural formula is:

Losartan potassium, USP is a white to off-white free-flowing crystalline powder with a molecular weight of 461.01. It is freely soluble in water, soluble in alcohols, and slightly soluble in common organic solvents, such as acetonitrile and methyl ethyl ketone.
Oxidation of the 5-hydroxymethyl group on the imidazole ring results in the active metabolite of losartan.
Hydrochlorothiazide is 6-chloro-3,4-dihydro-2H-1,2,4-benzothiadiazine-7-sulfonamide 1,1-dioxide. Its empirical formula is C7H8ClN3O4S2 and its structural formula is:

Hydrochlorothiazide, USP is a white, or practically white, crystalline powder with a molecular weight of 297.74, which is slightly soluble in water, but freely soluble in sodium hydroxide solution.
Losartan Potassium and Hydrochlorothiazide Tablets, USP are available for oral administration in three tablet combinations of losartan and hydrochlorothiazide. Losartan Potassium and Hydrochlorothiazide Tablets, USP 50 mg/12.5 mg contain 50 mg of losartan potassium USP and 12.5 mg of hydrochlorothiazide USP. Losartan Potassium and Hydrochlorothiazide Tablets, USP 100 mg/12.5 mg contain 100 mg of losartan potassium USP and 12.5 mg of hydrochlorothiazide USP. Losartan Potassium and Hydrochlorothiazide Tablets, USP 100 mg/25 mg contain 100 mg of losartan potassium USP and 25 mg of hydrochlorothiazide USP. Inactive ingredients are colloidal silicon dioxide, hydroxypropyl cellulose, hypromellose, lactose anhydrous, magnesium stearate, microcrystalline cellulose, pregelatinized starch, talc and titanium dioxide. Losartan Potassium and Hydrochlorothiazide Tablets, USP 50 mg/12.5 mg and Losartan Potassium and Hydrochlorothiazide Tablets, USP 100 mg/25 mg also contain D and C yellow No. 10 lake.
Losartan Potassium and Hydrochlorothiazide Tablets, USP 50 mg/12.5 mg contain 4.24 mg (0.108 mEq) of potassium, Losartan Potassium and Hydrochlorothiazide Tablets, USP 100 mg/12.5 mg contain 8.48 mg (0.216 mEq) of potassium, and Losartan Potassium and Hydrochlorothiazide Tablets, USP 100 mg/25 mg contain 8.48 mg (0.216 mEq) of potassium.

INDICATIONS AND USAGE

Hypertension

Losartan Potassium and Hydrochlorothiazide Tablets are indicated for the treatment of hypertension. This fixed dose combination is not indicated for initial therapy of hypertension, except when the hypertension is severe enough that the value of achieving prompt blood pressure control exceeds the risk of initiating combination therapy in these patients (see CLINICAL PHARMACOLOGY, Pharmacodynamics and Clinical Effects, and DOSAGE AND ADMINISTRATION).

Hypertensive Patients with Left Ventricular Hypertrophy

Losartan Potassium and Hydrochlorothiazide Tablets are indicated to reduce the risk of stroke in patients with hypertension and left ventricular hypertrophy, but there is evidence that this benefit does not apply to Black patients. (See PRECAUTIONS, Race, CLINICAL PHARMACOLOGY, Pharmacodynamics and Clinical Effects, Losartan Potassium, Reduction in the Risk of Stroke, Race, and DOSAGE AND ADMINISTRATION).

CONTRAINDICATIONS

Losartan Potassium and Hydrochlorothiazide Tablets are contraindicated in patients who are hypersensitive to any component of this product.

Because of the hydrochlorothiazide component, this product is contraindicated in patients with anuria or hypersensitivity to other sulfonamide-derived drugs.

ADVERSE REACTIONS

Losartan potassium-hydrochlorothiazide has been evaluated for safety in 858 patients treated for essential hypertension and 3889 patients treated for hypertension and left ventricular hypertrophy. In clinical trials with losartan potassium-hydrochlorothiazide, no adverse experiences peculiar to this combination have been observed. Adverse experiences have been limited to those that were reported previously with losartan potassium and/or hydrochlorothiazide. The overall incidence of adverse experiences reported with the combination was comparable to placebo.

In general, treatment with losartan potassium-hydrochlorothiazide was well tolerated. For the most part, adverse experiences have been mild and transient in nature and have not required discontinuation of therapy. In controlled clinical trials, discontinuation of therapy due to clinical adverse experiences was required in only 2.8% and 2.3% of patients treated with the combination and placebo, respectively.

In these double-blind controlled clinical trials, the following adverse experiences reported with losartan-hydrochlorothiazide occurred in ≥1 percent of patients, and more often on drug than placebo, regardless of drug relationship:

 | Losartan Potassium- Hydrochlorothiazide (n=858) | Placebo (n=173)
Body as a Whole
Abdominal pain | 1.2 | 0.6
Edema/swelling | 1.3 | 1.2
Cardiovascular
Palpitation | 1.4 | 0.0
Musculoskeletal
Back pain | 2.1 | 0.6
Nervous/Psychiatric
Dizziness | 5.7 | 2.9
Respiratory
Cough | 2.6 | 2.3
Sinusitis | 1.2 | 0.6
Upper respiratory infection | 6.1 | 4.6
Skin
Rash | 1.4 | 0.0

The following adverse events were also reported at a rate of 1% or greater, but were as, or more, common in the placebo group in studies of essential hypertension: asthenia/fatigue, diarrhea, nausea, headache, bronchitis, pharyngitis.

Adverse events occurred at about the same rates in men and women. Adverse events were somewhat more frequent in the elderly compared to non-elderly patients and somewhat more frequent in Blacks compared to non-Blacks for both the losartan-hydrochlorothiazide and the control groups.

A patient with known hypersensitivity to aspirin and penicillin, when treated with losartan potassium, was withdrawn from study due to swelling of the lips and eyelids and facial rash, reported as angioedema, which returned to normal 5 days after therapy was discontinued.

Superficial peeling of palms and hemolysis were reported in one subject treated with losartan potassium.

OVERDOSAGE

Losartan Potassium

Significant lethality was observed in mice and rats after oral administration of 1000 mg/kg and 2000 mg/kg, respectively, about 44 and 170 times the maximum recommended human dose on a mg/m^2 basis.

Limited data are available in regard to overdosage in humans. The most likely manifestation of overdosage would be hypotension and tachycardia; bradycardia could occur from parasympathetic (vagal) stimulation. If symptomatic hypotension should occur, supportive treatment should be instituted.

Neither losartan nor its active metabolite can be removed by hemodialysis.

Hydrochlorothiazide

The oral LD50 of hydrochlorothiazide is greater than 10 g/kg in both mice and rats. The most common signs and symptoms observed are those caused by electrolyte depletion (hypokalemia, hypochloremia, hyponatremia) and dehydration resulting from excessive diuresis. If digitalis has also been administered, hypokalemia may accentuate cardiac arrhythmias. The degree to which hydrochlorothiazide is removed by hemodialysis has not been established.

DOSAGE AND ADMINISTRATION

Hypertension

Dosing must be individualized. The usual starting dose of losartan is 50 mg once daily, with 25 mg recommended for patients with intravascular volume depletion (e.g., patients treated with diuretics) (see WARNINGS, Hypotension ─ Volume-Depleted Patients) and patients with a history of hepatic impairment (see WARNINGS, Impaired Hepatic Function). Losartan can be administered once or twice daily at total daily doses of 25 to 100 mg. If the antihypertensive effect measured at trough using once-a-day dosing is inadequate, a twice-a-day regimen at the same total daily dose or an increase in dose may give a more satisfactory response.

Hydrochlorothiazide is effective in doses of 12.5 to 50 mg once daily and can be given at doses of 12.5 to 25 mg as Losartan Potassium and Hydrochlorothiazide Tablets.

To minimize dose-independent side effects, it is usually appropriate to begin combination therapy only after a patient has failed to achieve the desired effect with monotherapy.

The side effects (see WARNINGS) of losartan are generally rare and apparently independent of dose; those of hydrochlorothiazide are a mixture of dose-dependent (primarily hypokalemia) and dose-independent phenomena (e.g., pancreatitis), the former much more common than the latter. Therapy with any combination of losartan and hydrochlorothiazide will be associated with both sets of dose-independent side effects.

Replacement Therapy: The combination may be substituted for the titrated components.

Dose Titration by Clinical Effect: A patient whose blood pressure is not adequately controlled with losartan monotherapy (see above) or hydrochlorothiazide alone, may be switched to Losartan Potassium and Hydrochlorothiazide Tablets 50 mg/12.5 mg (losartan 50 mg/hydrochlorothiazide 12.5 mg) once daily. If blood pressure remains uncontrolled after about 3 weeks of therapy, the dose may be increased to two tablets of Losartan Potassium and Hydrochlorothiazide 50 mg/12.5 mg once daily or one tablet of Losartan Potassium and Hydrochlorothiazide 100 mg/25 mg (losartan 100 mg/hydrochlorothiazide 25 mg) once daily. A patient whose blood pressure is not adequately controlled with losartan 100 mg monotherapy (see above) may be switched to Losartan Potassium and Hydrochlorothiazide Tablets 100 mg/12.5 mg once daily. If blood pressure remains uncontrolled after about 3 weeks of therapy, the dose may be increased to two tablets of Losartan Potassium and Hydrochlorothiazide 50 mg/12.5 mg once daily or one tablet of Losartan Potassium and Hydrochlorothiazide 100 mg/25 mg (losartan 100 mg/hydrochlorothiazide 25 mg) once daily.

A patient whose blood pressure is inadequately controlled by 25 mg once daily of hydrochlorothiazide, or is controlled but who experiences hypokalemia with this regimen, may be switched to Losartan Potassium and Hydrochlorothiazide Tablets 50 mg/12.5 mg (losartan 50 mg/hydrochlorothiazide 12.5 mg) once daily, reducing the dose of hydrochlorothiazide without reducing the overall expected antihypertensive response. The clinical response to Losartan Potassium and Hydrochlorothiazide Tablets 50 mg/12.5 mg should be subsequently evaluated, and if blood pressure remains uncontrolled after about 3 weeks of therapy, the dose may be increased to two tablets of Losartan Potassium and Hydrochlorothiazide Tablets 50 mg/12.5 mg once daily or one tablet of Losartan Potassium and Hydrochlorothiazide Tablets 100 mg/25 mg (losartan 100 mg/hydrochlorothiazide 25 mg) once daily.

The usual dose of Losartan Potassium and Hydrochlorothiazide is one tablet of Losartan Potassium and Hydrochlorothiazide 50 mg/12.5 mg once daily. More than two tablets of Losartan Potassium and Hydrochlorothiazide 50 mg/12.5 mg once daily or more than one tablet of Losartan Potassium and Hydrochlorothiazide 100 mg/25 mg once daily is not recommended. The maximal antihypertensive effect is attained about 3 weeks after initiation of therapy.

Use in Patients with Renal Impairment: The usual regimens of therapy with Losartan Potassium and Hydrochlorothiazide Tablets may be followed as long as the patient's creatinine clearance is >30 mL/min. In patients with more severe renal impairment, loop diuretics are preferred to thiazides, so Losartan Potassium and Hydrochlorothiazide Tablets are not recommended.

Patients with Hepatic Impairment: Losartan Potassium and Hydrochlorothiazide Tablets are not recommended for titration in patients with hepatic impairment (see WARNINGS, Impaired Hepatic function) because the appropriate 25 mg starting dose of losartan cannot be given.

Severe Hypertension

The starting dose of Losartan Potassium and Hydrochlorothiazide Tablets for initial treatment of severe hypertension is one tablet of Losartan Potassium and Hydrochlorothiazide 50 mg/12.5 mg once daily (see CLINICAL PHARMACOLOGY, Pharmacodynamics and Clinical Effects). For patients who do not respond adequately to Losartan Potassium and Hydrochlorothiazide Tablets 50 mg/12.5 mg after 2 to 4 weeks of therapy, the dosage may be increased to one tablet of Losartan Potassium and Hydrochlorothiazide 100 mg/25 mg once daily. The maximum dose is one tablet of Losartan Potassium and Hydrochlorothiazide 100 mg/25 mg once daily. Losartan Potassium and Hydrochlorothiazide Tablets are not recommended as initial therapy in patients with hepatic impairment (see WARNINGS, Impaired Hepatic Function) because the appropriate 25 mg starting dose of losartan cannot be given. It is also not recommended for use as initial therapy in patients with intravascular volume depletion (e.g., patients treated with diuretics, see WARNINGS, Hypotension ─ Volume-Depleted Patients).

Hypertensive Patients with Left Ventricular Hypertrophy

Treatment should be initiated with losartan potassium tablets 50 mg once daily. Hydrochlorothiazide 12.5 mg should be added or Losartan Potassium and Hydrochlorothiazide Tablets 50 mg/12.5 mg substituted if the blood pressure reduction is inadequate. If additional blood pressure reduction is needed, losartan potassium tablets 100 mg and hydrochlorothiazide 12.5 mg or Losartan Potassium and Hydrochlorothiazide Tablets 100 mg/12.5 mg may be substituted, followed by losartan potassium tablets 100 mg and hydrochlorothiazide 25 mg or Losartan Potassium and Hydrochlorothiazide Tablets 100 mg/25 mg. For further blood pressure reduction other antihypertensives should be added (see CLINICAL PHARMACOLOGY, Pharmacodynamics and Clinical Effects, Losartan Potassium, Reduction in the Risk of Stroke).

Losartan Potassium and Hydrochlorothiazide Tablets may be administered with other antihypertensive agents.

Losartan Potassium and Hydrochlorothiazide Tablets may be administered with or without food.

HOW SUPPLIED

Losartan Potassium and Hydrochlorothiazide Tablets, USP 100 mg/12.5 mg are white to off white colored, oval shaped, biconvex film coated tablets, debossed with "1117" on one side and plain on other side.

Bottles of 90 NDC 68258-6031-09

Storage

Store at 20° to 25°C (68° to 77°F) (See USP controlled room temperature). Protect from light.

Keep container tightly closed.

Manufactured by:

TORRENT PHARMACEUTICALS LTD., Indrad-382 721, Dist. Mehsana, INDIA.

For:

TORRENT PHARMA INC., 5380 Holiday Terrace, Suite 40, Kalamazoo, Michigan 49009.

Patient Information

Losartan Potassium and Hydrochlorothiazide Tablets, USP

100 mg/12.5 mg

Rx only

Read the Patient Information that comes with Losartan Potassium and Hydrochlorothiazide Tablets before you start taking it and each time you get a refill. There may be new information. This leaflet does not take the place of talking with your doctor about your condition and treatment.

What is the most important information I should know about Losartan Potassium and Hydrochlorothiazide Tablets?

Do not take Losartan Potassium and Hydrochlorothiazide Tablets if you are pregnant or plan to become pregnant. Losartan Potassium and Hydrochlorothiazide Tablets can harm your unborn baby causing injury and even death. Stop taking Losartan Potassium and Hydrochlorothiazide Tablets if you become pregnant and call your doctor right away. If you plan to become pregnant, talk to your doctor about other treatment options before taking Losartan Potassium and Hydrochlorothiazide Tablets.

What are Losartan Potassium and Hydrochlorothiazide Tablets?

Losartan Potassium and Hydrochlorothiazide Tablets contain 2 prescription medicines, an angiotensin receptor blocker (ARB) and a diuretic (water pill). It is used to:

- lower high blood pressure (hypertension). Losartan Potassium and Hydrochlorothiazide Tablets are not usually the first medicine used to treat high blood pressure.
- lower the chance of stroke in patients with high blood pressure and a heart problem called left ventricular hypertrophy (LVH). Losartan Potassium and Hydrochlorothiazide Tablets may not help Black patients with this problem.

Losartan Potassium and Hydrochlorothiazide Tablets have not been studied in children less than 18 years old.

High Blood Pressure (hypertension) Blood pressure is the force in your blood vessels when your heart beats and when your heart rests. You have high blood pressure when the force is too much. The losartan ingredient in Losartan Potassium and Hydrochlorothiazide Tablets can help your blood vessels relax so your blood pressure is lower. The hydrochlorothiazide ingredient in Losartan Potassium and Hydrochlorothiazide Tablets work by making your kidneys pass more water and salt.

Left Ventricular Hypertrophy (LVH) is an enlargement of the walls of the left chamber of the heart (the heart’s main pumping chamber). LVH can happen from several things. High blood pressure is the most common cause of LVH.

Who should not take Losartan Potassium and Hydrochlorothiazide Tablets?

Do not take Losartan Potassium and Hydrochlorothiazide Tablets if you:

- are allergic to any ingredients in Losartan Potassium and Hydrochlorothiazide Tablets. See a complete list of ingredients in Losartan Potassium and Hydrochlorothiazide Tablets at the end of this leaflet.
- are allergic to any sulfonamide-containing ("sulfa") medicines. Ask your doctor if you are not sure what sulfonamide-containing ("sulfa") medicines are.
- are not passing urine.

What should I tell my doctor before taking Losartan Potassium and Hydrochlorothiazide Tablets?

Tell your doctor about all your medical conditions including if you:

- are pregnant or planning to become pregnant. See "What is the most important information I should know about Losartan Potassium and Hydrochlorothiazide Tablets?"
- are breast-feeding or plan to breast-feed. Losartan potassium and hydrochlorothiazide tablets can pass into your milk and may harm your baby. You and your doctor should decide if you will take Losartan Potassium and Hydrochlorothiazide Tablets or breast-feed. You should not do both.
- have been vomiting (throwing up), having diarrhea, sweating a lot, or not drinking enough fluids. These could cause you to have low blood pressure.
- have liver problems
- have kidney problems
- have systemic lupus erythematosus (Lupus; SLE)
- have diabetes
- have asthma
- have gout
- have any allergies

Tell your doctor about all of the medicines you take, including prescription and non-prescription medicines, vitamins, and herbal supplements.

Losartan Potassium and Hydrochlorothiazide Tablets and certain other medicines may interact with each other. Especially tell your doctor if you are taking:

- potassium supplements
- salt substitutes containing potassium
- water pills (diuretics)
- lithium (a medicine used to treat a certain kind of depression)
- medicines used to treat pain and arthritis, called non-steroidal anti-inflammatory drugs (NSAIDs), including COX-2 inhibitors.
- other medicines to reduce blood pressure.

Know the medicines you take. Keep a list of your medicines and show it to your doctor and pharmacist when you get a new medicine.

How should I take Losartan Potassium and Hydrochlorothiazide Tablets?

- Take Losartan Potassium and Hydrochlorothiazide Tablets exactly as prescribed by your doctor. Your doctor may change your dose if needed.
- Losartan Potassium and Hydrochlorothiazide Tablets can be taken with or without food.
- If you miss a dose, take it as soon as you remember. If it is close to your next dose, do not take the missed dose. Just take the next dose at your regular time.
- If you take too much Losartan Potassium and Hydrochlorothiazide Tablets, call your doctor or Poison Control Center, or go to the nearest hospital emergency room right away.
- Your doctor may do blood tests from time to time while you are taking Losartan Potassium and Hydrochlorothiazide Tablets.

What are the possible side effects of Losartan Potassium and Hydrochlorothiazide Tablets?

Losartan Potassium and Hydrochlorothiazide Tablets may cause the following side effects that may be serious:

- injury or death of unborn babies. See "What is the most important information I should know about Losartan Potassium and Hydrochlorothiazide Tablets?"
- allergic reaction. Symptoms of an allergic reaction are swelling of the face, lips, throat, or tongue. Get emergency medical help right away and stop taking Losartan Potassium and Hydrochlorothiazide Tablets.
- low blood pressure (hypotension). Low blood pressure may cause you to feel faint or dizzy. Lie down if you feel faint or dizzy. Call your doctor right away.
- a new or worsening condition called systemic lupus erythematosus (Lupus; SLE)
- If you have kidney problems, you may see a worsening in how well your kidneys work. Call your doctor if you get swelling in your feet, ankles, or hands, or unexplained weight gain.
- If you have liver problems, you may see a worsening in how well your liver works. Call your doctor if you get nausea, pain in the right upper stomach area (abdomen), yellow eyes or skin (which can be itchy).
- Eye problems. One of the medicines in Losartan Potassium and Hydrochlorothiazide Tablets can cause eye problems that, if left untreated, may lead to vision loss. Symptoms of eye problems can happen within hours to weeks of starting Losartan Potassium and Hydrochlorothiazide Tablets.

Tell your doctor right away if you have:

○ decrease in vision

○ eye pain

The most common side effects of Losartan Potassium and Hydrochlorothiazide Tablets in people with high blood pressure are:

- "colds" (upper respiratory infection)
- dizziness
- stuffy nose
- back pain
- fast or irregular heartbeat (palpitations)
- rash

Tell your doctor if you get any side effect that bothers you or that won't go away. This is not a complete list of side effects. For a complete list, ask your doctor or pharmacist.

Call your doctor for medical advice about side effects. You may report side effects to FDA at 1-800-FDA-1088.

How should I store Losartan Potassium and Hydrochlorothiazide Tablets?

- Store Losartan Potassium and Hydrochlorothiazide Tablets at 20° to 25°C (68° to 77°F) (See USP controlled room temperature).
- Keep Losartan Potassium and Hydrochlorothiazide Tablets in a tightly closed container, and keep Losartan Potassium and Hydrochlorothiazide Tablets out of the light.
- Keep Losartan Potassium and Hydrochlorothiazide Tablets and all medicines out of the reach of children.

General information about Losartan Potassium and Hydrochlorothiazide Tablets

Medicines are sometimes prescribed for conditions that are not mentioned in patient information leaflets. Do not use Losartan Potassium and Hydrochlorothiazide Tablets for a condition for which it was not prescribed. Do not give Losartan Potassium and Hydrochlorothiazide Tablets to other people, even if they have the same symptoms that you have. It may harm them.

This leaflet summarizes the most important information about Losartan Potassium and Hydrochlorothiazide Tablets. If you would like more information, talk with your doctor. You can ask your pharmacist or doctor for information that is written for health professionals.

What are the ingredients in Losartan Potassium and Hydrochlorothiazide Tablets?

Active ingredients: losartan potassium, USP and hydrochlorothiazide, USP
Inactive ingredients: colloidal silicon dioxide, hydroxypropyl cellulose, hypromellose, lactose anhydrous, magnesium stearate, microcrystalline cellulose, pregelatinized starch, talc and titanium dioxide. Losartan Potassium and Hydrochlorothiazide Tablets, USP 50 mg/12.5 mg and Losartan Potassium and Hydrochlorothiazide Tablets, USP 100 mg/25 mg also contain D and C yellow No. 10 lake.

Manufactured by:

TORRENT PHARMACEUTICALS LTD., Indrad-382 721, Dist. Mehsana, INDIA.

For:

TORRENT PHARMA INC., 5380 Holiday Terrace, Suite 40, Kalamazoo, Michigan 49009.

PRINCIPAL DISPLAY PANEL

NDC 68258-6031-XX

NDC 68258-6031-09